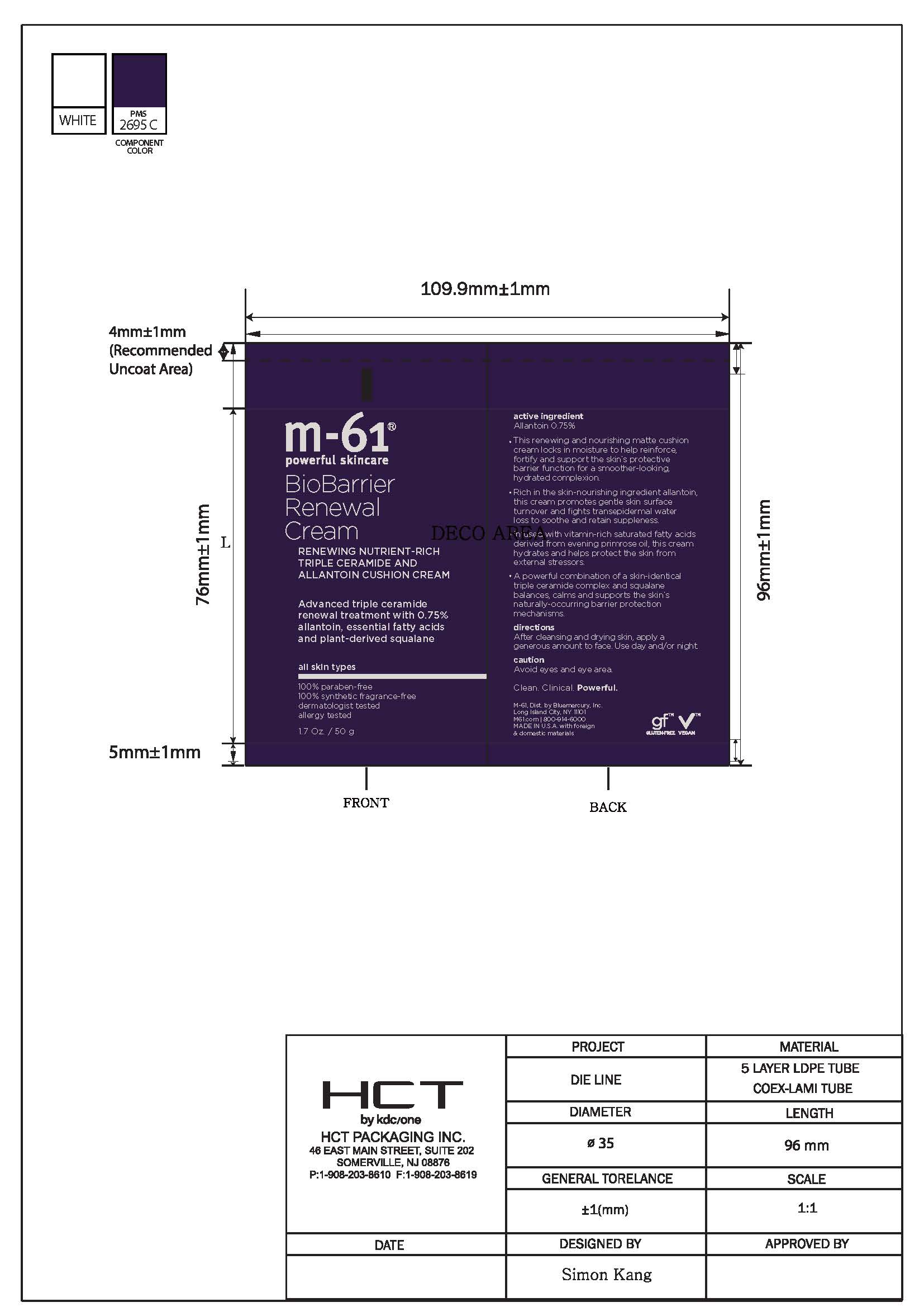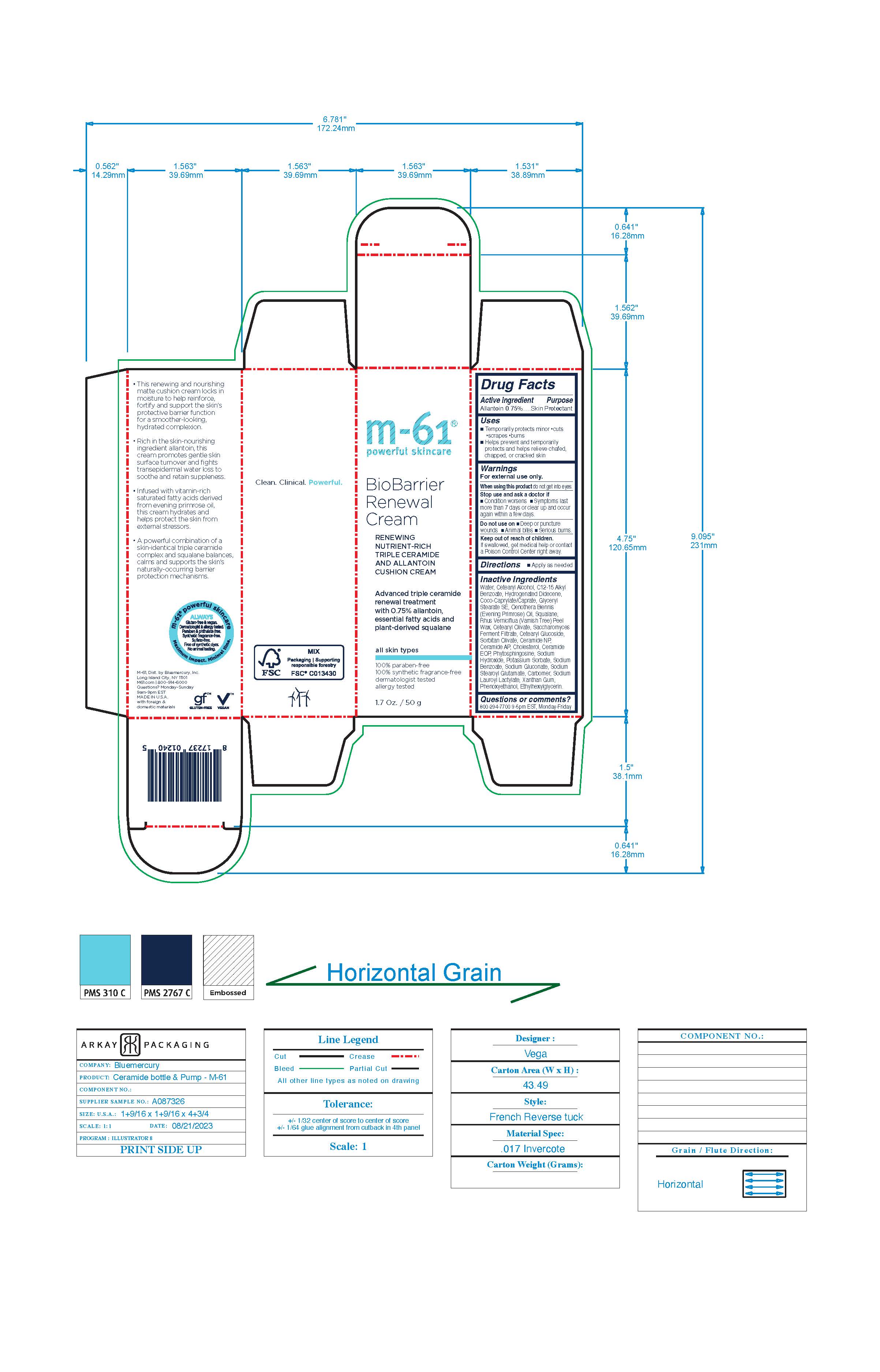 DRUG LABEL: BioBarrier Renewal Cream
NDC: 72203-019 | Form: CREAM
Manufacturer: bluemercury
Category: otc | Type: HUMAN OTC DRUG LABEL
Date: 20240915

ACTIVE INGREDIENTS: ALLANTOIN 7.5 mg/1 g
INACTIVE INGREDIENTS: ALKYL (C12-15) BENZOATE; HYDROGENATED DIDECENE; COCO-CAPRYLATE/CAPRATE; EVENING PRIMROSE OIL; TOXICODENDRON VERNICIFLUUM FRUIT RIND WAX; CETEARYL OLIVATE; SODIUM BENZOATE; GLYCERYL STEARATE SE; SODIUM HYDROXIDE; PHYTOSPHINGOSINE; CERAMIDE NP; CHOLESTEROL; CARBOMER HOMOPOLYMER, UNSPECIFIED TYPE; SODIUM LAUROYL LACTYLATE; ETHYLHEXYLGLYCERIN; SORBITAN OLIVATE; SODIUM GLUCONATE; WATER; CETOSTEARYL ALCOHOL; SQUALANE; CERAMIDE AP; SACCHAROMYCES CEREVISIAE; CETEARYL GLUCOSIDE; CERAMIDE 1; POTASSIUM SORBATE; SODIUM STEAROYL GLUTAMATE; XANTHAN GUM; PHENOXYETHANOL

M-61 BioBarrier Renewal Cream

m-61

powerful skincare

BioBarrier

Renewal

Cream

RENEWING

NUTRIENT-RICH

TRIPLE CERAMIDE

AND ALLANTOIN

CUSHION CREAM

Advanced triple ceramide
renewal treatment
with 0.75% allantoin,
essential fatty acids and
plant-derived squalane

all skin types

100% paraben-free
100% synthetic fragrance-free
dermatologist tested
allergy tested

1.7 Oz. / 50 g

Active Ingredients

Active Ingredient

Allantoin 0.75%

Purpose

Skin Protectant

Uses

- Temporarily protects minor cuts, scrapes, burns
  - Helps prevent and temporarily protects and helps relieve chaged, chapped, or cracked skin

WARNINGS

For external use only.

When using this product do not get into eyes.

Stop use and ask a doctor if

- Conition worsens
- Symptoms last more than 7 days or clear up and occur again within a few days.

Do not use on

- Deep or puncture wounds
- Animal bites
- Serious burns.

Keep out of reach of children

If swallowed, get medical help or contact
a Poison Control Center right away.

Directions

- Apply as needed

Inactive Ingredients

Water, Cetearyl Alcohol, C12-15 Alkyl Benzoate, Hydrogenated Didecene, Coco-Caprylate/Caprate, Glyceryl Stearate SE, Oenothera Biennis (Evening Primrose) Oil, Squalane, Rhus Verniciflua (Varnish Tree) Peel Wax, Cetearyl Olivate, Saccharomyces Ferment Filtrate, Cetearyl Glucoside, Sorbitan Olivate, Ceramide NP, Ceramide AP, Cholesterol, Ceramide EOP, Phytosphingosine, Sodium Hydroxide, Potassium Sorbate, Sodium Benzoate, Sodium Gluconate, Sodium Stearoyl Glutamate, Carbomer, Sodium Lauroyl Lactylate, Xanthan Gum, Phenoxyethanol, Ethylhexylglycerin.

Questions or comments?

800-294-7700 9-5pm EST, Monday-Friday